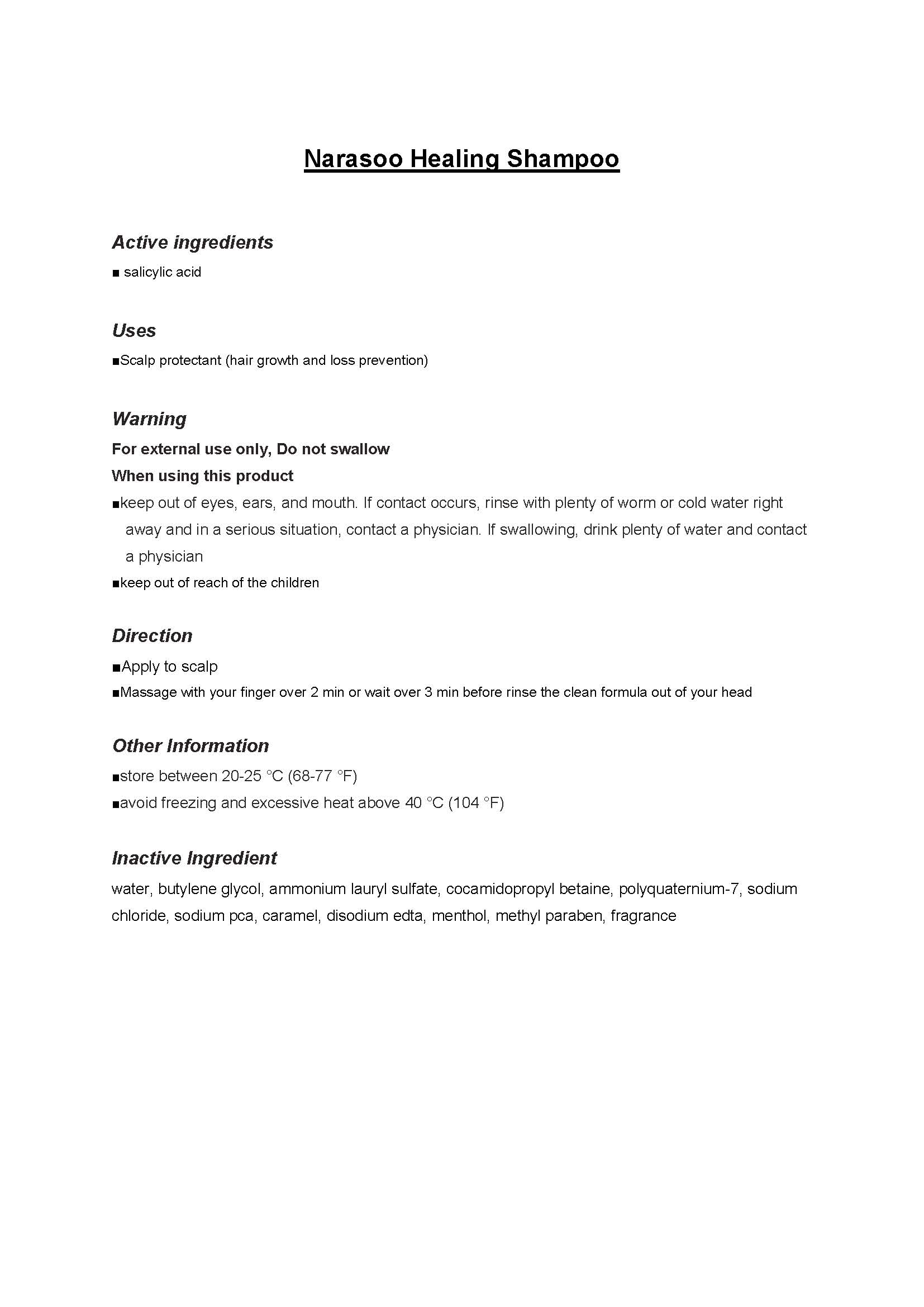 DRUG LABEL: Narasoo Healing
NDC: 69114-1001 | Form: SHAMPOO
Manufacturer: RAKU STORY Co., Ltd
Category: otc | Type: HUMAN OTC DRUG LABEL
Date: 20140717

ACTIVE INGREDIENTS: SALICYLIC ACID 0.06 g/1 mL
INACTIVE INGREDIENTS: BUTYLENE GLYCOL; MENTHOL; WATER

Drug Facts

ACTIVE INGREDIENT

salicylic acid

INACTIVE INGREDIENT

water, butylene glycol, ammonium lauryl sulfate, cocamidopropyl betaine, polyquaternium-7, sodium chloride, sodium pca, caramel, disodium edta, menthol, methyl paraben, fragrance

PURPOSE

hair loss prevention and hair grower

keep out of reach of the children

INDICATIONS AND USAGE

apply a proper amount on the scalp and massage with your finger

- do not use the product on wounds or areas with abnomalities such as eczema and inflammation
- storage and handling
make sure to close the lid after use
keep away from children and infants
store away from too high or low temperatures and direct sunlight

DOSAGE AND ADMINISTRATION

for external use only